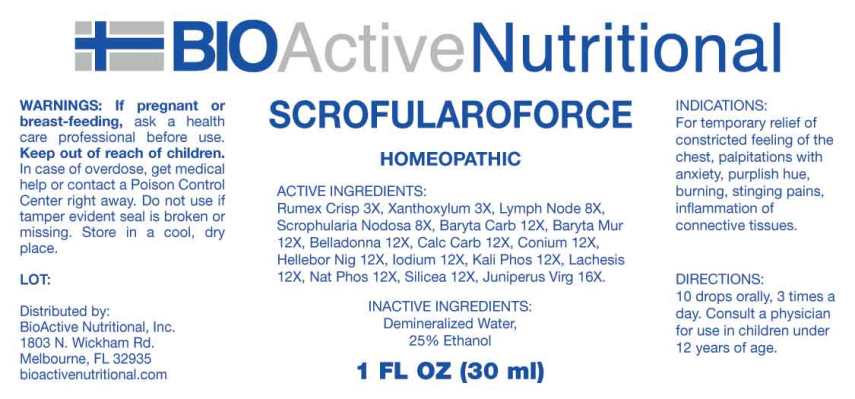 DRUG LABEL: Scrofularoforce
NDC: 43857-0580 | Form: LIQUID
Manufacturer: BioActive Nutritional, Inc.
Category: homeopathic | Type: HUMAN OTC DRUG LABEL
Date: 20240912

ACTIVE INGREDIENTS: RUMEX CRISPUS ROOT 3 [hp_X]/1 mL; ZANTHOXYLUM AMERICANUM BARK 3 [hp_X]/1 mL; SUS SCROFA LYMPH 8 [hp_X]/1 mL; SCROPHULARIA NODOSA WHOLE 8 [hp_X]/1 mL; BARIUM CARBONATE 12 [hp_X]/1 mL; BARIUM CHLORIDE DIHYDRATE 12 [hp_X]/1 mL; ATROPA BELLADONNA 12 [hp_X]/1 mL; OYSTER SHELL CALCIUM CARBONATE, CRUDE 12 [hp_X]/1 mL; CONIUM MACULATUM FLOWERING TOP 12 [hp_X]/1 mL; HELLEBORUS NIGER ROOT 12 [hp_X]/1 mL; IODINE 12 [hp_X]/1 mL; DIBASIC POTASSIUM PHOSPHATE 12 [hp_X]/1 mL; LACHESIS MUTA VENOM 12 [hp_X]/1 mL; SODIUM PHOSPHATE, DIBASIC, HEPTAHYDRATE 12 [hp_X]/1 mL; SILICON DIOXIDE 12 [hp_X]/1 mL; JUNIPERUS VIRGINIANA TWIG 16 [hp_X]/1 mL
INACTIVE INGREDIENTS: WATER; ALCOHOL

DRUG FACTS:

ACTIVE INGREDIENTS:

Rumex Crispus 3X, Xanthoxylum Fraxineum 3X, Lymph Node (Suis) 8X, Scrophularia Nodosa 8X Baryta Carbonica 12X, Baryta Muriatica 12X, Belladonna 12X, Calcarea Carbonica 12X, Conium Maculatum 12X, Helleborus Niger 12X, Iodium 12X, Kali Phosphoricum 12X, Lachesis Mutus 12X, Natrum Phosphoricum 12X, Silicea 12X, Juniperus Virginiana 16X.

INDICATIONS:

For temporary relief of constricted feeling of the chest, palpitations with anxiety, purplish hue, burning, stinging pains, inflammation of connective tissues.

WARNINGS:

If pregnant or breast-feeding, ask a health care professional before use.

Keep out of reach of children. In case of overdose, get medical help or contact a Poison Control Center right away.

Do not use if tamper evident seal is broken or missing.

Store in cool, dry place.

KEEP OUT OF REACH OF CHILDREN:

In case of overdose, get medical help or contact a Poison Control Center right away.

DIRECTIONS:

10 drops orally, 3 times a day. Consult a physician for use in children under 12 years of age.

INDICATIONS:

For temporary relief of constricted feeling of the chest, palpitations with anxiety, purplish hue, burning, stinging pains, inflammation of connective tissues.

INACTIVE INGREDIENTS:

Demineralized Water, 25% Ethanol.

QUESTIONS:

Distributed by:
BioActive Nutritional, Inc.
1803 N. Wickham Rd.
Melbourne, FL 32935
bioactivenutritional.com

PACKAGE LABEL DISPLAY:

BIOActive Nutritional

SCROFULAROFORCE

HOMEOPATHIC

1 FL OZ (30 ml)